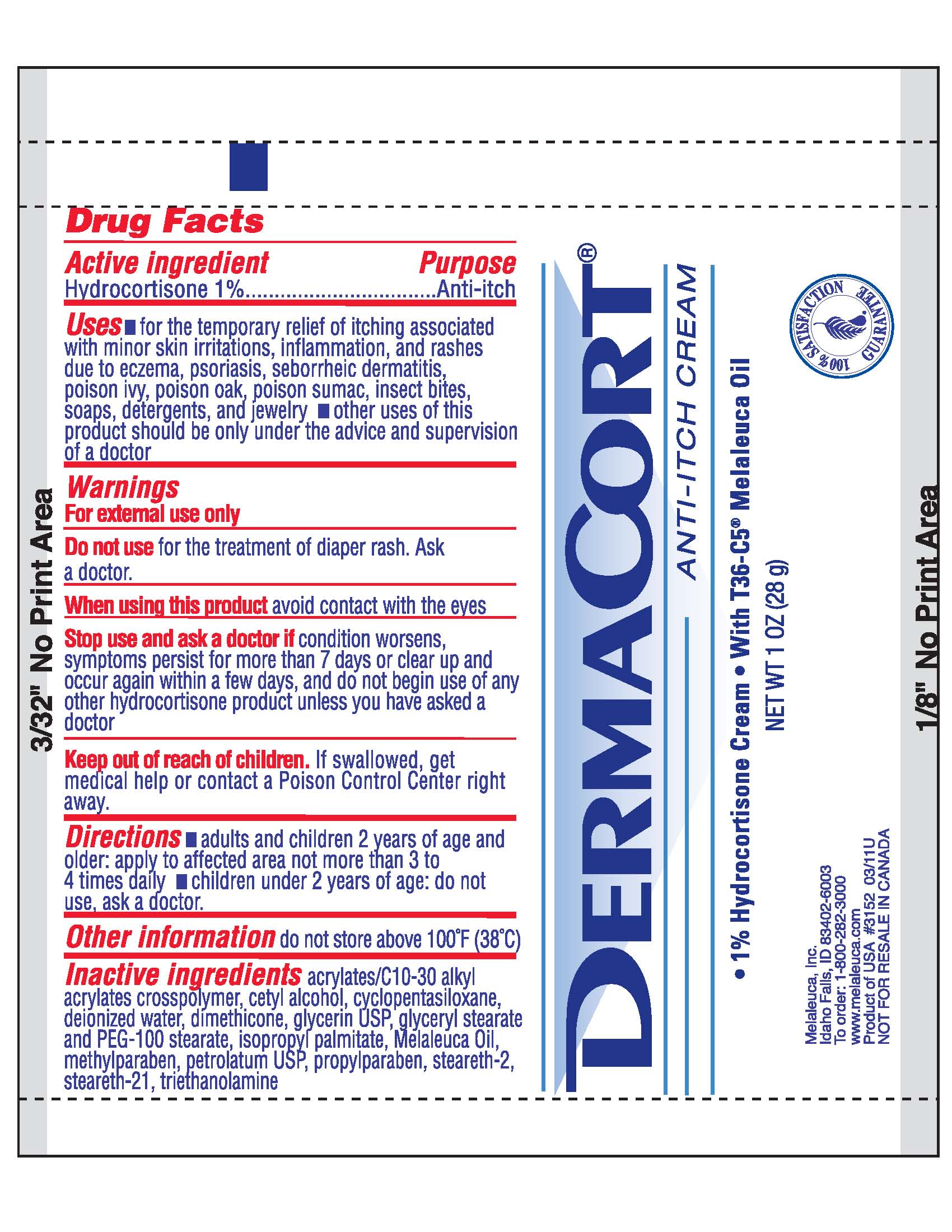 DRUG LABEL: DermaCort
NDC: 54473-117 | Form: CREAM
Manufacturer: Melaleuca, Inc.
Category: otc | Type: HUMAN OTC DRUG LABEL
Date: 20111109

ACTIVE INGREDIENTS: HYDROCORTISONE 10 mg/1 g
INACTIVE INGREDIENTS: CARBOMER COPOLYMER TYPE B (ALLYL PENTAERYTHRITOL CROSSLINKED); CETYL ALCOHOL; CYCLOMETHICONE 5; DIMETHICONE; GLYCERIN; GLYCERYL MONOSTEARATE; ISOPROPYL PALMITATE; METHYLPARABEN; PETROLATUM; POLYOXYL 100 STEARATE; PROPYLPARABEN; STEARETH-2; STEARETH-21; TEA TREE OIL; TROLAMINE; WATER

Dermacort Anti-Itch Cream content of label

Active ingredient
Hydrocortisone 1%

Purpose
Anti-itch

Uses

- for the temporary relief of itching associated with minor skin irritations, inflammation, and rashes due to eczema, psoriasis, seborrheic dermatitis, poison ivy, poison oak, poison sumac, insect bites, soaps, detergents, and jewelry
- other uses of this product should be only under the advice and supervision of a doctor

Warnings
For external use only

Do not use for the treatment of diaper rash. Ask a doctor.

When using this product avoid contact with the eyes

Stop use and ask a doctor if condition worsens, symptoms persist for more than 7 days or clear up and occur again within a few days, and do not begin use of any other hydrocortisone product unless you have asked a doctor

Keep out of reach of children. If swallowed, get medical help or contact a Poison Control Center right away.

Directions

- adults and children 2 years of age and older: apply to affected area not more than 3 to 4 times daily
- children under 2 years of age: do not use, ask a doctor.

Other information do not store above 100°F (38°C)

INACTIVE INGREDIENT

Inactive ingredients acrylates/C10-30 alkyl acrylates crosspolymer, cetyl alcohol, cyclopentasiloxane, deionized water, dimethicone, glycerin USP, glyceryl stearate and PEG-100 stearate, isopropyl palmitate, Melaleuca Oil, methylparaben, petrolatum USP, propylparaben, steareth-2, steareth-21, triethanolamine